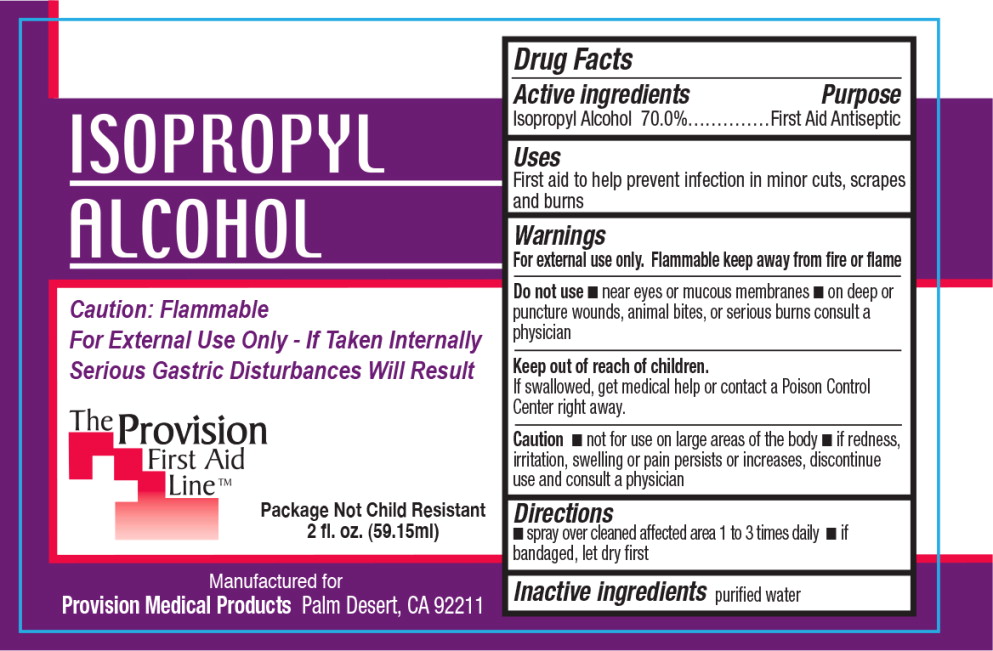 DRUG LABEL: Isopropyl Alcohol
NDC: 69103-3502 | Form: SPRAY
Manufacturer: Provision Medical
Category: otc | Type: HUMAN OTC DRUG LABEL
Date: 20140829

ACTIVE INGREDIENTS: isopropyl alcohol 700 mL/1 L
INACTIVE INGREDIENTS: water

Drug Facts

Active ingredients

Isopropyl Alcohol 70.0%

Purpose

First Aid Antiseptic

Uses

First aid to help prevent infection in minor cuts, scrapes and burns

Warnings

For external use only. Flammable keep away from fire or flame

Do not use

- near eyes or mucous membranes
- on deep or puncture wounds, animal bites, or serious burns consult a physician

Keep out of reach of children.

If swallowed, get medical help or contact a Poison Control Center right away.

Caution

- not for use on large areas of the body
- if redness, irritation, swelling or pain persists or increases, discontinue use and consult a physician

Directions

- spray over cleaned affected area 1 to 3 times daily
- if bandaged, let dry first

Inactive ingredients

purified water

Principal Display Panel - Bottle Label

ISOPROPYL
ALCOHOL

Caution: Flammable

For External Use Only - If Taken Internally
Serious Gastric Disturbances Will Result

Package Not Child Resistant

2 fl. oz. (59.15ml)

Manufactured for

Provision Medical Products Palm Desert, CA 92211